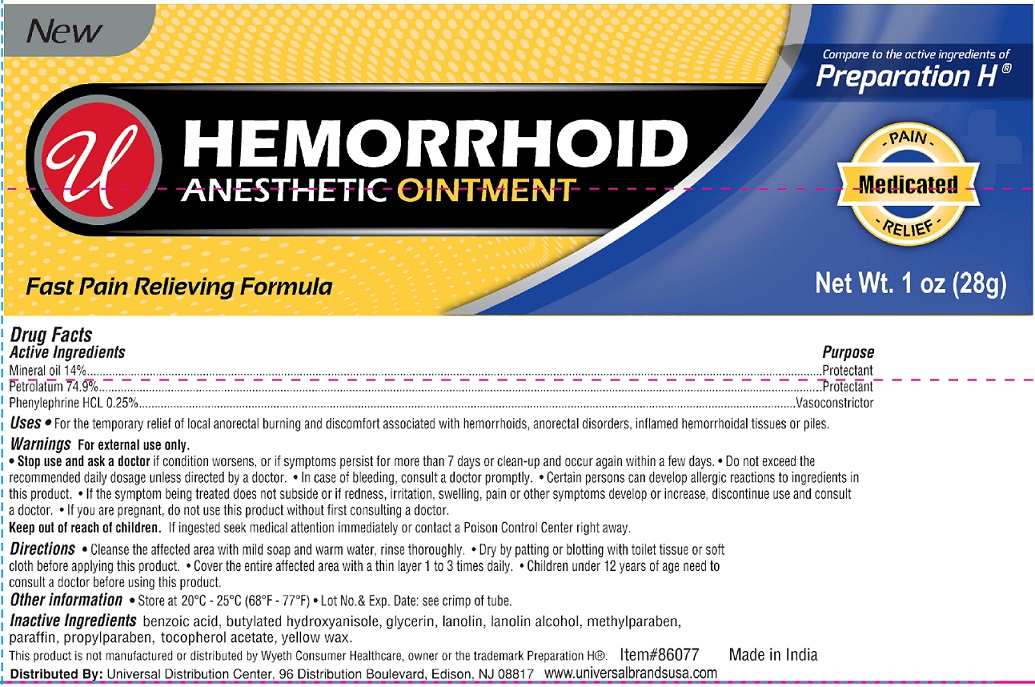 DRUG LABEL: Hemorrhoid Anesthetic
NDC: 52000-057 | Form: OINTMENT
Manufacturer: Universal Distribution Center LLC
Category: otc | Type: HUMAN OTC DRUG LABEL
Date: 20251030

ACTIVE INGREDIENTS: MINERAL OIL 0.14 g/1 g; PETROLATUM 0.749 g/1 g; PHENYLEPHRINE HYDROCHLORIDE 0.0025 g/1 g
INACTIVE INGREDIENTS: BENZOIC ACID; BUTYLATED HYDROXYANISOLE; GLYCERIN; LANOLIN; LANOLIN ALCOHOLS; METHYLPARABEN; PARAFFIN; PROPYLPARABEN; .ALPHA.-TOCOPHEROL ACETATE; YELLOW WAX

Hemorrhoid Anesthetic Ointment

Active Ingredients

Mineral Oil 14%

Petrolatum 74.9%

Phenylephrine HCL 0.25%

Purpose

Protectant

Protectant

Vasoconstrictor

Uses

- For the temporary relief of local anorectal burning and discomfort associated with hemmorrhoids, anorectal disorders, inflamed hemorrhoidal tissues or piles.

Warnings

For external use only.

- Stop use and ask a doctorif condition worsens, or if symptoms persist for more than 7 days or clean-up and occur again within a few days.
- Do not exceed the recommended daily dosage unless directed by a doctor.
- In case of bleeding, consult a doctor promptly.
- Certain persons can develop allergic reactions to ingredients in this product.
- If the symptom being treated does not subside or if redness, irritation, swelling, pain or other symptoms develop or increase, discontinue use and consult a doctor.
- If you are pregnant, do not use this product without first consulting a doctor.

Keep out of reach of children.

If ingested seek medical attention immediately or contact a Poison Control Center right away.

Directions

- Cleanse the affected area with mild soap and warm water, rinse thoroughly.
- Dry by patting or blotting with toilet tissue or soft cloth before applying this product.
- Cover the entire affected area with a thin layer 1 to 3 times daily.
- Children under 12 years of age need to consult a doctor before using this product.

Other Information

- Store at 20ºC to 25ºC (68ºF to 77ºF)
- Lot No. & Exp. Date: see crimp of tube.

Inactive Ingredients

benzoic acid, butylated hydroxyanisole, glycerin, lanolin, lanolin alcohol, methylparaben, paraffin, propylparaben, tocopherol acetate, yellow wax.

PACKAGE LABEL

PRINCIPAL DISPLAY PANEL

Hemorrhoid Anesthetic Ointment

NET WT. 1 OZ. (28 g)